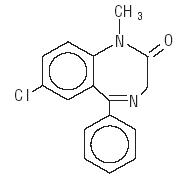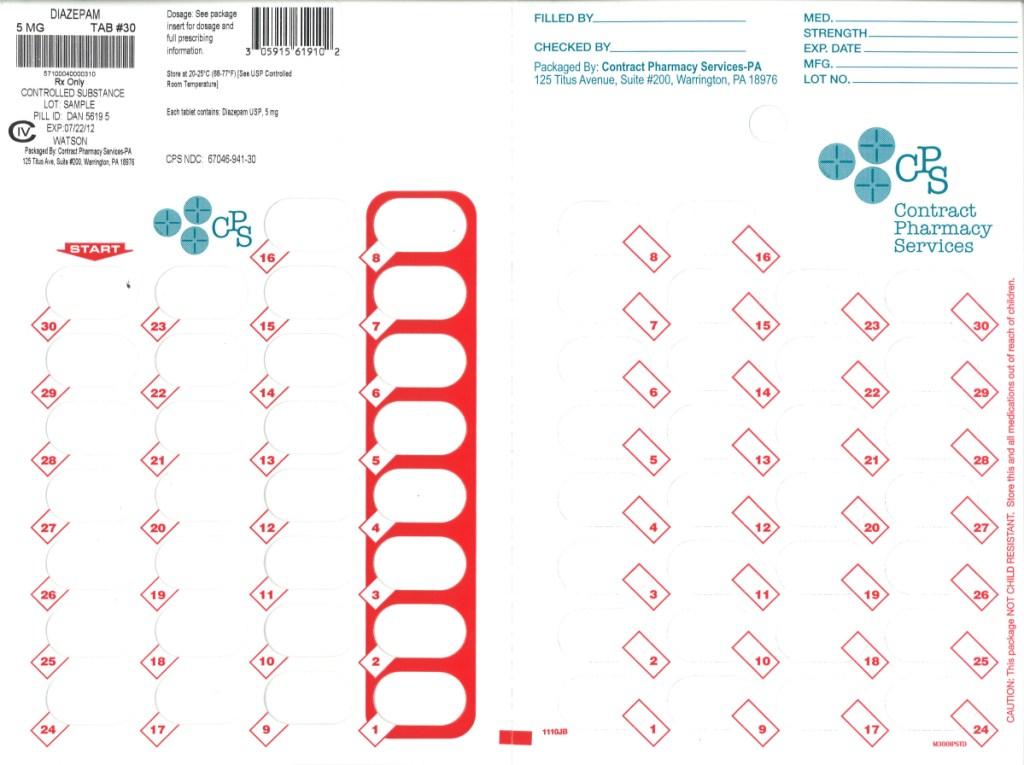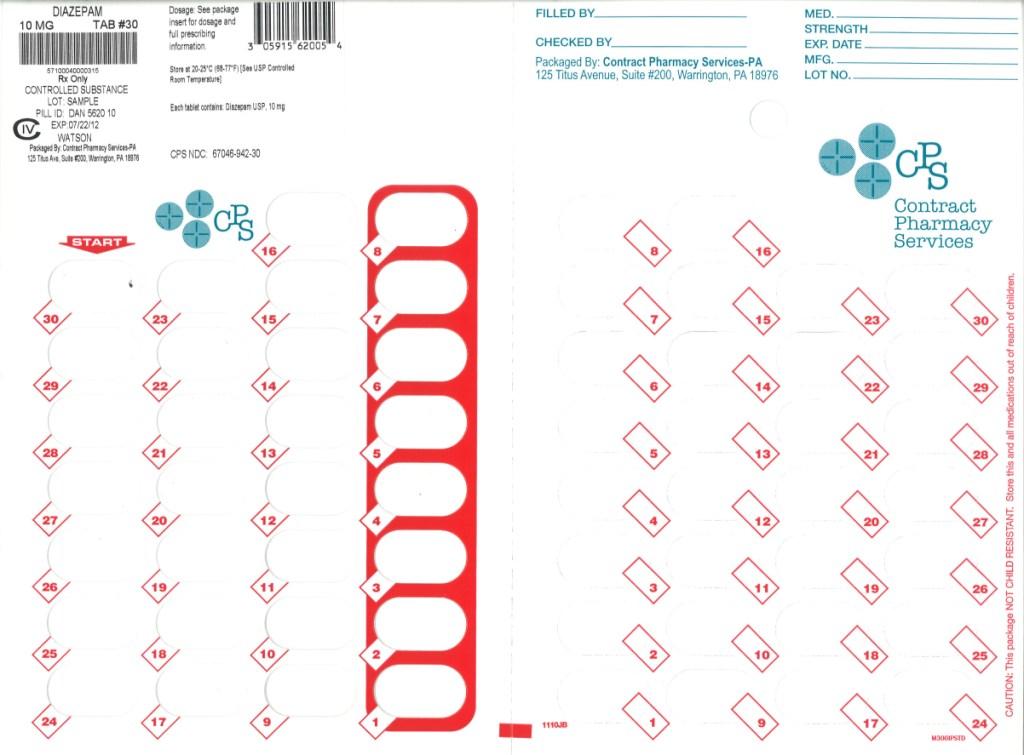 DRUG LABEL: Diazepam
NDC: 67046-942 | Form: TABLET
Manufacturer: Contract Pharmacy Services-PA
Category: prescription | Type: HUMAN PRESCRIPTION DRUG LABEL
Date: 20110801
DEA Schedule: CIV

ACTIVE INGREDIENTS: Diazepam 10 mg/1 1
INACTIVE INGREDIENTS: ANHYDROUS LACTOSE; magnesium stearate; CELLULOSE, MICROCRYSTALLINE; FD&C BLUE NO. 1

Diazepam
Tablets USP C-IV
Rx only

DESCRIPTION

Diazepam is a benzodiazepine derivative. Chemically, diazepam is 7-Chloro-1,3-dihydro-1-methyl-5-phenyl-2H-1,4-benzodiazepin-2-one. It is a colorless crystalline compound, and is insoluble in water. The structural formula is represented below:

C16H13ClN2O M.W. 284.74

Diazepam Tablets USP 2 mg, 5 mg and 10 mg, for oral administration, contain the following inactive ingredients: anhydrous lactose, magnesium stearate and microcrystalline cellulose.

Diazepam Tablets USP 5 mg also contain D&C Yellow No. 10.

Diazepam Tablets USP 10 mg also contain FD&C Blue No. 1.

PHARMACOLOGY

In animals, diazepam appears to act on parts of the limbic system, the thalamus and hypothalamus, and induces calming effects. Diazepam, unlike chlorpromazine and reserpine, has no demonstrable peripheral autonomic blocking action, nor does it produce extrapyramidal side effects; however, animals treated with diazepam do have a transient ataxia at higher doses. Diazepam was found to have transient cardiovascular depressor effects in dogs. Long-term experiments in rats revealed no disturbances of endocrine function.

Oral LD50 of diazepam is 720 mg/kg in mice and 1240 mg/kg in rats. Intraperitoneal administration of 400 mg/kg to a monkey resulted in death on the sixth day.

Reproduction Studies

A series of rat reproduction studies was performed with diazepam in oral doses of 1, 10, 80 and 100 mg/kg. At 100 mg/kg there was a decrease in the number of pregnancies and surviving offspring in these rats. Neonatal survival of rats at doses lower than 100 mg/kg was within normal limits. Several neonates in these rat reproduction studies showed skeletal or other defects. Further studies in rats at doses up to and including 80 mg/kg/day did not reveal teratological effects on the offspring.

In humans, measurable blood levels of diazepam were obtained in maternal and cord blood, indicating placental transfer of the drug.

INDICATIONS

Diazepam Tablets USP are indicated for the management of anxiety disorders or for the short-term relief of the symptoms of anxiety. Anxiety or tension associated with the stress of everyday life usually does not require treatment with an anxiolytic.

In acute alcohol withdrawal, diazepam may be useful in the symptomatic relief of acute agitation, tremor, impending or acute delirium tremens and hallucinosis.

Diazepam is a useful adjunct for the relief of skeletal muscle spasm due to reflex spasm to local pathology (such as inflammation of the muscles or joints, or secondary to trauma); spasticity caused by upper motor neuron disorders (such as cerebral palsy and paraplegia); athetosis; and stiff-man syndrome.

Oral diazepam may be used adjunctively in convulsive disorders, although it has not proved useful as the sole therapy.

The effectiveness of diazepam in long-term use, that is, more than 4 months, has not been assessed by systematic clinical studies. The physician should periodically reassess the usefulness of the drug for the individual patient.

CONTRAINDICATIONS

Diazepam Tablets USP are contraindicated in patients with a known hypersensitivity to this drug and, because of lack of sufficient clinical experience, in children under 6 months of age. It may be used in patients with open angle glaucoma who are receiving appropriate therapy, but is contraindicated in acute narrow angle glaucoma.

WARNINGS

Diazepam is not of value in the treatment of psychotic patients and should not be employed in lieu of appropriate treatment. As is true of most preparations containing CNS-acting drugs, patients receiving diazepam should be cautioned against engaging in hazardous occupations requiring complete mental alertness such as operating machinery or driving a motor vehicle.

As with other agents which have anticonvulsant activity, when diazepam is used as an adjunct in treating convulsive disorders, the possibility of an increase in the frequency and/or severity of grand mal seizures may require an increase in the dosage of standard anticonvulsant medication. Abrupt withdrawal of diazepam in such cases may also be associated with a temporary increase in the frequency and/or severity of seizures.

Since diazepam has a central nervous system depressant effect, patients should be advised against the simultaneous ingestion of alcohol and other CNS-depressant drugs during diazepam therapy.

Usage in Pregnancy

An increased risk of congenital malformations associated with the use of minor tranquilizers (diazepam, meprobamate and chlordiazepoxide) during the first trimester of pregnancy has been suggested in several studies. Because use of these drugs is rarely a matter of urgency, their use during this period should almost always be avoided. The possibility that a woman of childbearing potential may be pregnant at the time of institution of therapy should be considered. Patients should be advised that if they become pregnant during therapy or intend to become pregnant they should communicate with their physicians about the desirability of discontinuing the drug.

Management of Overdosage

Manifestations of diazepam overdosage include somnolence, confusion, coma and diminished reflexes. Respiration, pulse and blood pressure should be monitored, as in all cases of drug overdosage, although, in general, these effects have been minimal following overdosage. General supportive measures should be employed, along with immediate gastric lavage. Intravenous fluids should be administered and an adequate airway maintained. Hypotension may be combated by the use of norepinephrine or metaraminol. Dialysis is of limited value. As with the management of intentional overdosage with any drug, it should be borne in mind that multiple agents may have been ingested.

Flumazenil, a specific benzodiazepine receptor antagonist, is indicated for the complete or partial reversal of the sedative effects of benzodiazepines and may be used in situations when an overdose with a benzodiazepine is known or suspected. Prior to the administration of flumazenil, necessary measures should be instituted to secure airway, ventilation, and intravenous access. Flumazenil is intended as an adjunct to, not as a substitute for, proper management of benzodiazepine overdose. Patients treated with flumazenil should be monitored for re-sedation, respiratory depression, and other residual benzodiazepine effects for an appropriate period after treatment. The prescriber should be aware of a risk of seizure in association with flumazenil treatment, particularly in long-term benzodiazepine users and in cyclic antidepressant overdose. The complete flumazenil package insert including CONTRAINDICATIONS, WARNINGS and PRECAUTIONS should be consulted prior to use.

Withdrawal symptoms of the barbiturate type have occurred after the discontinuation of benzodiazepines (see DRUG ABUSE AND DEPENDENCE section).

PRECAUTIONS

If diazepam is to be combined with other psychotropic agents or anticonvulsant drugs, careful consideration should be given to the pharmacology of the agents to be employed — particularly with known compounds which may potentiate the action of diazepam, such as phenothiazines, narcotics, barbiturates, MAO inhibitors and other antidepressants. The usual precautions are indicated for severely depressed patients or those in whom there is any evidence of latent depression; particularly the recognition that suicidal tendencies may be present and protective measures may be necessary. The usual precautions in treating patients with impaired renal or hepatic function should be observed.

In elderly and debilitated patients, it is recommended that the dosage be limited to the smallest effective amount to preclude the development of ataxia or oversedation (2 mg to 2 ½ mg once or twice daily, initially, to be increased gradually as needed and tolerated).

The clearance of diazepam and certain other benzodiazepines can be delayed in association with Tagamet (cimetidine) administration. The clinical significance of this is unclear.

Information for Patients

To assure the safe and effective use of benzodiazepines, patients should be informed that, since benzodiazepines may produce psychological and physical dependence, it is advisable that they consult with their physician before either increasing the dose or abruptly discontinuing this drug.

ADVERSE REACTIONS

Side effects most commonly reported were drowsiness, fatigue and ataxia. Infrequently encountered were confusion, constipation, depression, diplopia, dysarthria, headache, hypotension, incontinence, jaundice, changes in libido, nausea, changes in salivation, skin rash, slurred speech, tremor, urinary retention, vertigo and blurred vision. Paradoxical reactions such as acute hyperexcited states, anxiety, hallucinations, increased muscle spasticity, insomnia, rage, sleep disturbances and stimulation have been reported; should these occur, use of the drug should be discontinued.

Because of isolated reports of neutropenia and jaundice, periodic blood counts and liver function tests are advisable during long-term therapy. Minor changes in EEG patterns, usually low-voltage fast activity, have been observed in patients during and after diazepam therapy and are of no known significance.

DRUG ABUSE AND DEPENDENCE

Diazepam tablets are classified by the Drug Enforcement Administration as a schedule IV controlled substance.

Withdrawal symptoms, similar in character to those noted with barbiturates and alcohol (e.g., convulsions, tremor, abdominal and muscle cramps, vomiting and sweating), have occurred following abrupt discontinuance of diazepam. The more severe withdrawal symptoms have usually been limited to those patients who received excessive doses over an extended period of time. Generally milder withdrawal symptoms (e.g., dysphoria and insomnia) have been reported following abrupt discontinuance of benzodiazepines taken continuously at therapeutic levels for several months. Consequently, after extended therapy, abrupt discontinuation should generally be avoided and a gradual dosage tapering schedule followed. Addiction-prone individuals (such as drug addicts or alcoholics) should be under careful surveillance when receiving diazepam or other psychotropic agents because of the predisposition of such patients to habituation and dependence.

DOSAGE AND ADMINISTRATION

Dosage should be individualized for maximum beneficial effect. While the usual daily dosages given below will meet the needs of most patients, there will be some who may require higher doses. In such cases, dosage should be increased cautiously to avoid adverse effects.

Adults: | Usual Daily Dose
Management of Anxiety Disorders and relief of Symptoms of Anxiety. | Depending on severity of symptoms — 2 mg to 10 mg, 2 to 4 times daily
Symptomatic Relief in Acute Alcohol Withdrawal. | 10 mg, 3 or 4 times during the first 24 hours, reducing to 5 mg, 3 or 4 times daily as needed
Adjunctively for Relief of Skeletal Muscle Spasm. | 2 mg to 10 mg, 3 or 4 times daily
Adjunctively in Convulsive Disorders | 2 mg to 10 mg, 2 to 4 times daily
Geriatric Patients, or in the presence of debilitating disease. | 2 mg to 2 ½ mg, 1 or 2 times daily initially; increase gradually as needed and tolerated
Children:
Because of varied responses to CNS-acting drugs, initiate therapy with lowest dose and increase as required. Not for use in children under 6 months. | 1 mg to 2 ½ mg, 3 or 4 times daily initially; increase gradually as needed and tolerated

HOW SUPPLIED

Diazepam Tablets USP 2 mg are scored, round, white tablets imprinted DAN 5621 and 2 supplied in bottles of 100, 500 and 1000.

Diazepam Tablets USP 5 mg are scored, round, yellow tablets imprinted DAN 5619 and 5 supplied in bottles of 100, 500 and 1000.

Diazepam Tablets USP 10 mg are scored, round, blue tablets imprinted DAN 5620 and 10 supplied in bottles of 100, 500 and 1000.

Dispense in tight, light-resistant container with child-resistant closure.

Store at 20°-25°C (68°-77°F). [See USP controlled room temperature.]

Watson Laboratories, Inc.
Corona, CA 92880 USA

Repackaged by:
Contract Pharmacy Services-PA
125 Titus Ave Suite 200
Warrington, PA 18976 USA

Original--3/2011--NJW

Updated--08/2011--NJW

PRINCIPAL DISPLAY PANEL

10 mg Blister of 30

PRINCIPAL DISPLAY PANEL

5 mg Blister of 30